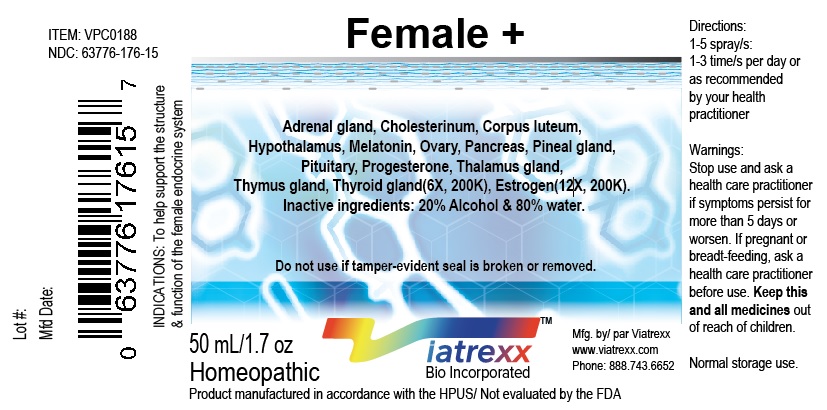 DRUG LABEL: Female Plus
NDC: 63776-176 | Form: SPRAY
Manufacturer: VIATREXX BIO INCORPORATED
Category: homeopathic | Type: HUMAN OTC DRUG LABEL
Date: 20191227

ACTIVE INGREDIENTS: Bos Taurus Adrenal Gland 200 [kp_C]/1 mL; Sus Scrofa Adrenal Gland 200 [kp_C]/1 mL; Cholesterol 200 [kp_C]/1 mL; Sus Scrofa Corpus Luteum 200 [kp_C]/1 mL; Estrogens, Esterified 200 [kp_C]/1 mL; Bos Taurus Hypothalamus 200 [kp_C]/1 mL; Sus Scrofa Hypothalamus 200 [kp_C]/1 mL; Melatonin 200 [kp_C]/1 mL; Bos Taurus Ovary 200 [kp_C]/1 mL; Sus Scrofa Ovary 200 [kp_C]/1 mL; Bos Taurus Pancreas 200 [kp_C]/1 mL; Sus Scrofa Pancreas 200 [kp_C]/1 mL; Bos Taurus Pineal Gland 200 [kp_C]/1 mL; Sus Scrofa Pineal Gland 200 [kp_C]/1 mL; Bos Taurus Pituitary Gland 200 [kp_C]/1 mL; Sus Scrofa Pituitary Gland 200 [kp_C]/1 mL; Progesterone 200 [kp_C]/1 mL; Sus Scrofa Thalamus 200 [kp_C]/1 mL; Bos Taurus Thymus 200 [kp_C]/1 mL; Sus Scrofa Thymus 200 [kp_C]/1 mL; Thyroid, Bovine 200 [kp_C]/1 mL; Thyroid, Porcine 200 [kp_C]/1 mL
INACTIVE INGREDIENTS: Alcohol; Water

Female +

Active Ingredients

Adrenal gland 6X 200K, Cholesterinum 6X 200K, Corpus luteum 6X 200K, Estrogen 12X 200K, Hypothalamus 6X 200K, Melatonin 6X 200K, Ovary 6X 200K, Pancreas 6X 200K, Pineal gland 6X 200K, Pituitary 6X 200K, Progesterone 6X 200K, Thalamus Gland 6X 200K, Thymus gland 6X 200K, Thyroid gland 6X 200K

Purpose

Adrenal gland | Adrenal support
Cholesterinum | Drainage
Corpus luteum | Regeneration
Estrogen | Hormonal support
Hypothalamus | Regeneration
Melatonin | Neurological support
Ovary | Regeneration
Pancreas | Regeneration
Pineal gland | Regeneration
Pituitary | Regeneration
Progesterone | Hormonal support
Thalamus Gland | Regeneration
Thymus gland | Regeneration
Thyroid gland | Regeneration

Uses

To help support the structure & function of the female endocrine system

Warnings

Stop use and ask a health care practitioner if symptoms persist for more than five days or worsen. If pregnant or breastfeeding, ask a health care practitioner before use.

Dosage

1-3 spray(s); 1-3 time(s) per day or as recommended by your healthcare practitioner.

KEEP OUT OF REACH OF CHILDREN

Keep this and all medicines out of reach of children.

Other Ingredients

Alcohol and Water

Other Information

Normal storage use.
Do not use if tamper-evident seal is broken or removed.

Questions

info@viatrexx.com

Principal Display Panel

ITEM: VPC0187
NDC 63776-176-15
Homeopathic remedy
Female +
• To help support the structure & function of the female endocrine system
Oral spray
50ml 1.7 oz
Viatrexx™ Bio Incorporated
Manufactured by Viatrexx
www.viatrexx.com
Newark, DE 19713

Female +
50 mL
1.7 oz
Viatrexx™ Bio Incorporated
ITEM: VPC0187
NDC: 63776-176-14
INDICATIONS:
To help support the structure & function of the female endocrine system
DIRECTIONS:
1-5 spray(s); 1-3 time(s) per day or as recommended by your health care practitioner.
Mfg. for
Viatrexx Bio Incorporated.
www.viatrexx.com
Newark, DE 19713